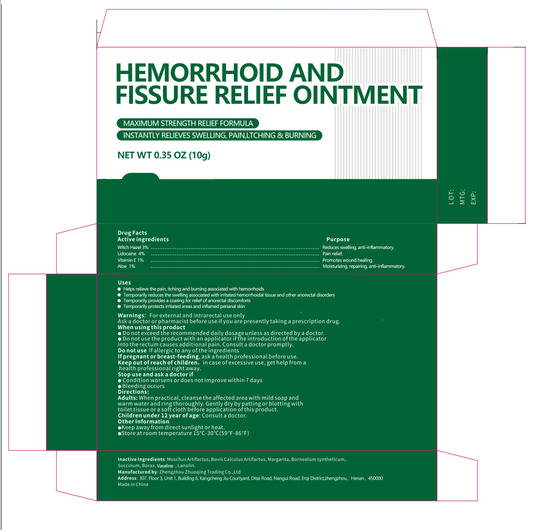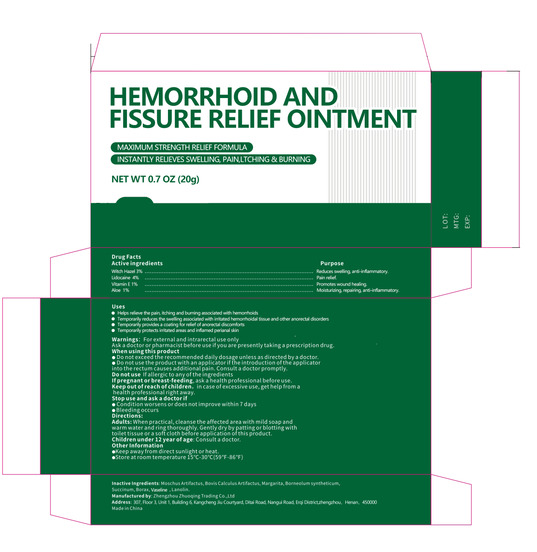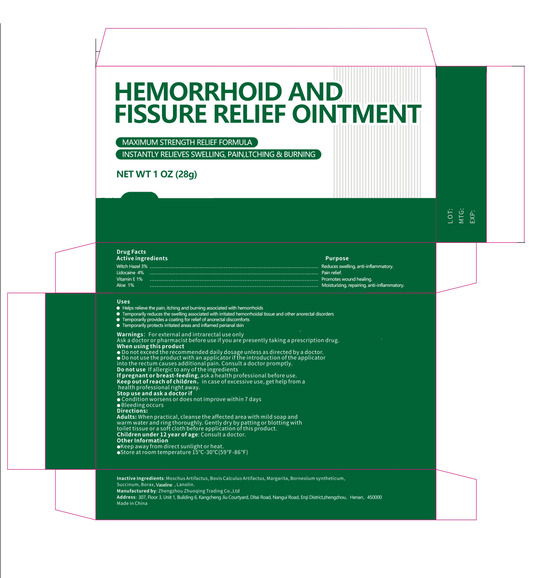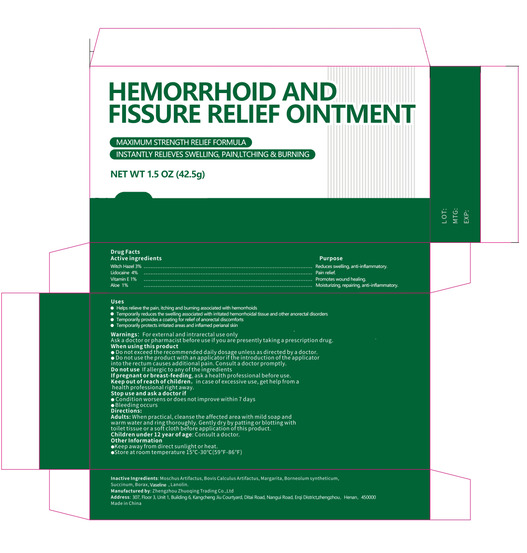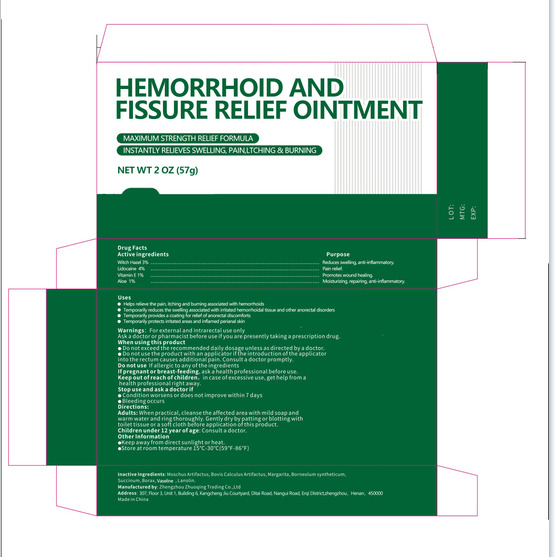 DRUG LABEL: Hemorrhoid and Fissure Relief
NDC: 83632-003 | Form: PASTE
Manufacturer: Zhengzhou Zhuoqing Trading Co., Ltd.
Category: otc | Type: HUMAN OTC DRUG LABEL
Date: 20250226

ACTIVE INGREDIENTS: ALPHA-TOCOPHEROL 1 g/100 g; ALOE 1 g/100 g; LIDOCAINE 4 g/100 g; WITCH HAZEL 3 g/100 g
INACTIVE INGREDIENTS: ANAPHALIS MARGARITACEA LEAF; AMBER; BORNEOL; SODIUM BORATE; PETROLATUM; SUCCINIC ACID; BILIRUBIN; MOSKENE

83632-003
Hemorrhoid and Fissure Relief Ointment

Active ingredients

Witch Hazel 3%
Lidocaine 4%
Vitamin E 1%
Aloe 1%

PURPOSE

Reduces swelling, anti-iflammatory.
Pain relief.
Promotes wound healing.
Moisturizing, repairing, ant-infammatory

Uses

1.Helps relieve the pain, itching and bumning associated with hemorrhoids
2.Temporarily reduces the swelling associated with iritated hemorrhoidal tissue and other anorectal disorders
3.Temporarily provides a coating for relief of anorectal discomforts
4.Temporarily protects imitated areas and infamed perianal skin

Warnings: For external and intrarectal use only
Ask a doctor or pharmacist before use if you are presently taking a prescription drug.

DO not use If allergic to any of the ingredients
If pregnant or breast-feeding, ask a health professional before use.

When usina this product

●DO not exceed the recommended daily dosage unless as directed by a doctor.
●Do not use the product with an applicator if the introduction of the applicator
into the rectum Causes additional pain. Consult a doctor promptly.

STOP USE

●Condition worsens or does not improve within 7 days
●Bleeding occurs

Keep out of reach of children, in case of excessive use, get help from a health professional right away.

Directions

Adults: When practical, cleanse the affected area with mild soap and warm water and ring thoroughly. Gently dry by patting or blotting with toilet tissue or a soft cloth before application of this product.

Children under 12 year of age: Consult a doctor.

Other Information

●Keep away from direct sunlight or heat.
●Store at room temperature 15C-30°C(59°F-86°F)

Inactive Ingredients

Inactive Ingredients: Moschus Artifactus, Bovis Calculus Artifactus, Margarita, Borneolum syntheticum,
Succinum, Borax, Vaseline， L anolin.